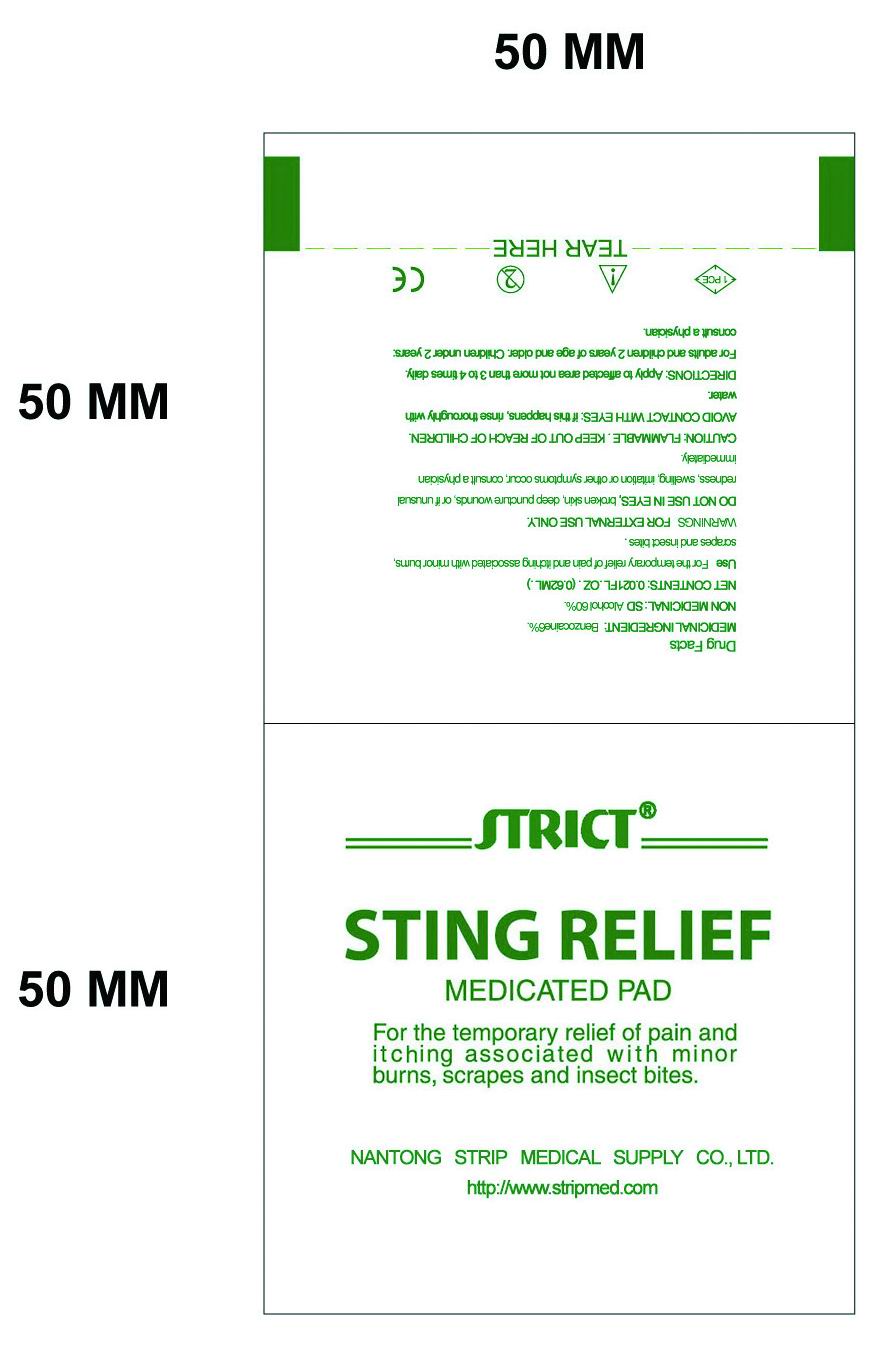 DRUG LABEL:  Sting Relief
NDC: 35617-395 | Form: SWAB
Manufacturer: NANTONG STRIP MEDICAL SUPPLY CO.,LTD.
Category: otc | Type: HUMAN OTC DRUG LABEL
Date: 20100526

ACTIVE INGREDIENTS: Benzocaine 0.06 mL/1 1; Alcohol 0.6 mL/1 1
INACTIVE INGREDIENTS: WATER

Drug Fact

Active Ingredient

Medicinal Ingredient:Benzocaine6%, NON MEDICINAL: SD Alcohol 60%.

Use

For the temporary relief of pain and itching associated with minor burns, scrapes and insect bites

Directions

Apply to affected area not more than 3 to 4 times daily. For adults and children 2 years of age and older. Children under 2 years: consult a physician. DO NOT USE IN EYES, broken skin, deep puncture wounds, or if unusual redness, swelling, irritation or other symptoms occur, consult a physician immediately

Cautions

FLAMMABLE.KEEP OUT OF REACH OF CHILDREN. FOR EXTERNAL USE ONLY. AVOID CONTACT WITH EYES: if this happens, rinse thoroughly with water.

Inactive Ingredients

purified water